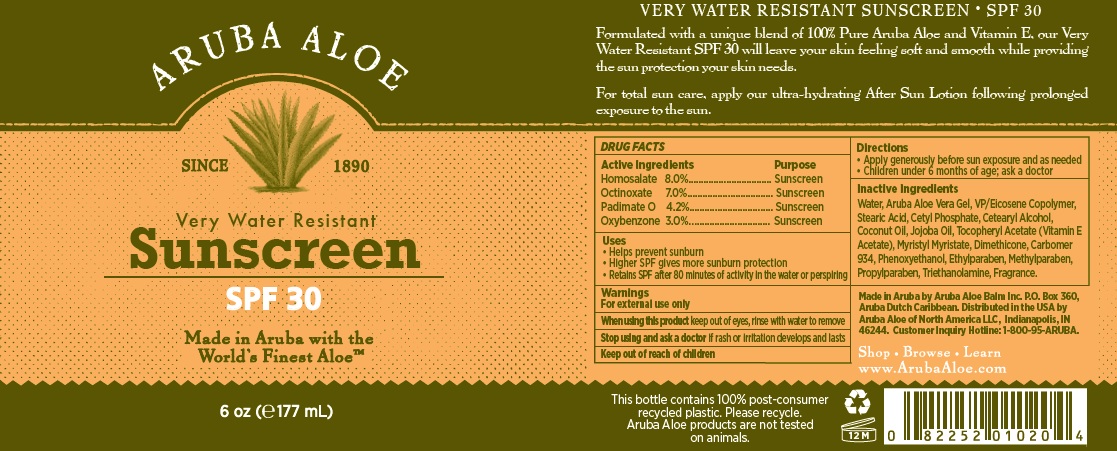 DRUG LABEL: Aruba Aloe Very Water Resistant Sunscreen
NDC: 53675-150 | Form: LOTION
Manufacturer: Aruba Aloe Balm, NV
Category: otc | Type: HUMAN OTC DRUG LABEL
Date: 20231114

ACTIVE INGREDIENTS: HOMOSALATE 80 mg/1 mL; OCTINOXATE 70 mg/1 mL; PADIMATE O 42 mg/1 mL; OXYBENZONE 30 mg/1 mL
INACTIVE INGREDIENTS: WATER; ALOE VERA LEAF; STEARIC ACID; CETYL PHOSPHATE; CETOSTEARYL ALCOHOL; COCONUT OIL; JOJOBA OIL; ACETATE ION; MYRISTYL MYRISTATE; DIMETHICONE; CARBOMER 934; PHENOXYETHANOL; ETHYLPARABEN; METHYLPARABEN; PROPYLPARABEN; TROLAMINE

Aruba Aloe Very Water Resistant Sunscreen SPF

Active Ingredients

Homosalate 8.0%

Octinoxate 7.0%

Padimate O 4.2%

Oxybenzone 3.0%

Purpose

Sunscreen

Uses

- Helps prevent sunburn
- Higher SPF gives more sunburn protection
- Retains SPF after 80minutes of activity in the water

Warnings

For external use only/

When using this product

keep out of eyes, rinse with water to remove

Stop using and ask a doctor

if rash or irritation develops and lasts

Keep out of reach of children

Directions

Apply generously before sun exposure and as needed

Children under 6 months of age; ask a doctor

Inactive Ingredients

Water, Aruba Aloe Vera gel, VP/Eicosene Copolymer, stearic acid, cetyl phosphate, cetearyl alcohol, coconut oil, jojoba oil, tocopheryl acetate (Vitamin E Acetate), myristyl myristate, dimethicone, carbomer 934, phenoxyethanol, ethlparabven, methylparaben, propylparaben, triethanolamine, fragrance

Made in Aruba by Aruba Aloe Balm, Inc

PO Box 360, Aruba Dutch Caribbean. Distributed in the USA by Aruba Aloe of North America, LLC, Indianapolis, IN 46244. Customer inquiry Hotline: 1-800-95 ARUBA

Shop Browse Learn

www.arubaaloe.com

DESCRIPTION

VERY WATER RESISTANT SUNSCREEN SPF 30

Formulate with a unique blend of 100% Pure Aruba Aloe and Vitamin E, our Very Water Resistant SPF 30 will leave your skin feeling soft and smooth while providing the sun protection your skin needs.

For total sun care, apply our ultra-hydrating After Sun Lotion following prolonged exposure to the sun.

This bottle contains 100% post consumer recycled plastic. Please recycle. Aruba Aloe products are not tested on animals.

PACKAGE LABEL

ARUBA ALOE

since 1890

Very Water Resistant

Sunscreen SPF 30

Made in Aruba with the Worlds Finest Aloe (tm)

6oz (177mL)